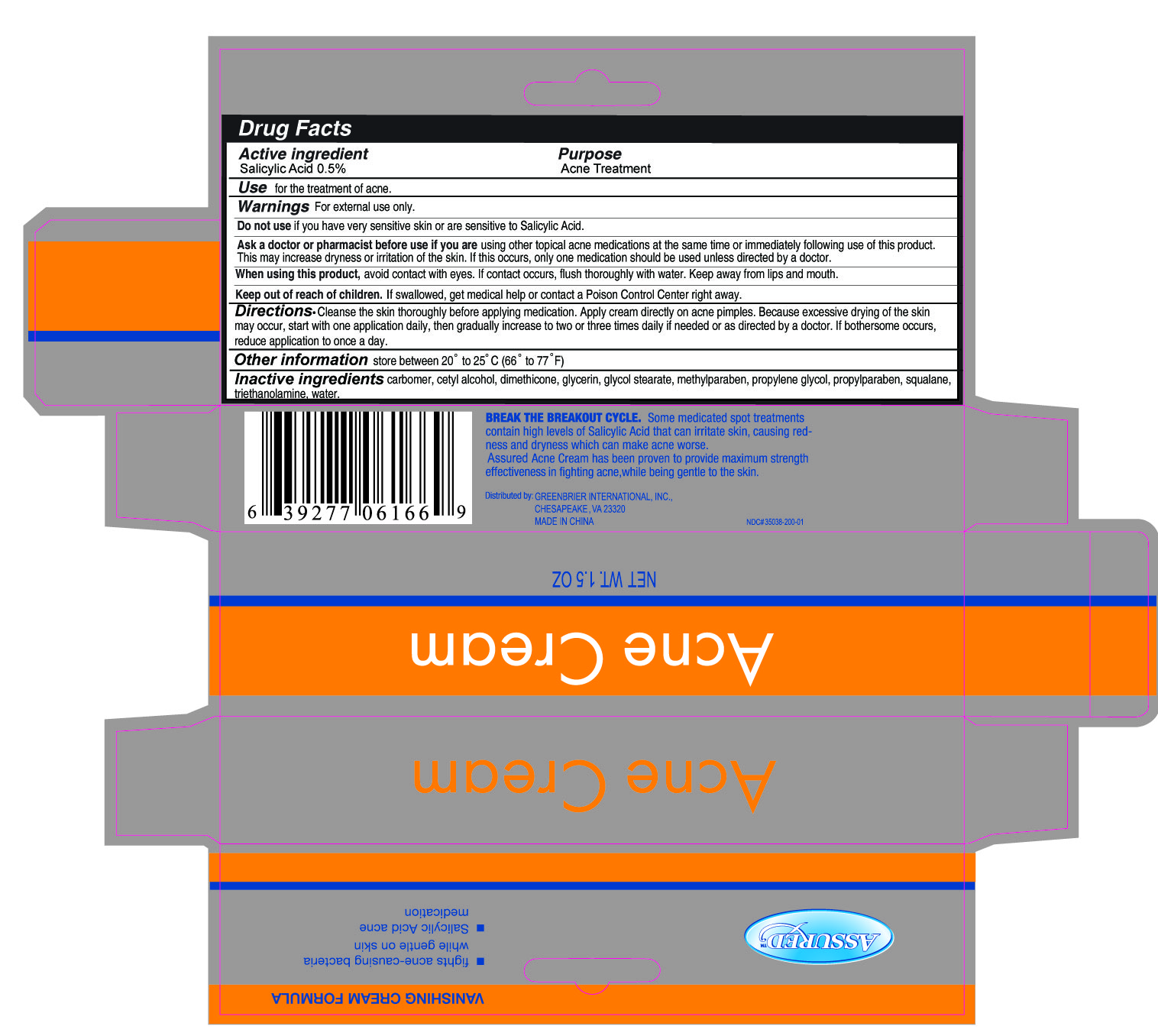 DRUG LABEL: ASSURED ACNE CREAM
NDC: 35038-200 | Form: CREAM
Manufacturer: HANGZHOU MINO DAILY CHEMICALS CO.LTD.
Category: otc | Type: HUMAN OTC DRUG LABEL
Date: 20101215

ACTIVE INGREDIENTS: SALICYLIC ACID .5 mL/100 mL
INACTIVE INGREDIENTS: WATER 74.5 mL/100 mL; SQUALANE 10 mL/100 mL; PROPYLENE GLYCOL 5 mL/100 mL; CETYL ALCOHOL 3.5 mL/100 mL; GLYCERIN 3 mL/100 mL; GLYCOL STEARATE 2 mL/100 mL; DIMETHICONE 1 mL/100 mL; METHYLPARABEN .2 mL/100 mL; PROPYLPARABEN .1 mL/100 mL; TROLAMINE .1 mL/100 mL

Drug Facts

Active Ingredient

Salicylic Acid 0.5%

Purpose

Acne Treatment

Warnings

For external use only

- flammable, keep away from fire and flame
- will produce serious gastric disturbances if taken internally

Ask a doctor before use if you have deep puncture wounds or serious burns

When using this product

- do not get into eyes or mucous membranes
- use only in a well-ventilated area

Stop use and ask a doctor if condition persists or gets worse.

Keep out of reach of children. In case of an accidental ingestion, contact a Poison Control Center immediately.

Use

for the treatment of acne.

WARNINGS

For external use only.

Do not use if you have very sensitive skin or are sensitive to Salicylic Acid.

Ask a doctor or pharmacist before use if you are using other topical acne medications at the same time or immediately following use of this product. This may increase dryness or irritation of the skin. If this occurs, only one medication should be used unless directed by a doctor.

When using this product, avoid contact with eyes. If contact occurs, flush thoroughly with water. Keep away from lips and mouth.

Keep out of reach of children. If swallowed, get medical help or contact a Poison Control Center right away.

Directions

Cleanse the skin thoroughly before applying medication. Apply cream directly on acne pimples. Because excessive drying of the skin may occur, start with one application daily, then gradually increase to two or three times daily if needed or as directed by a doctor. If bothersome occurs, reduce application to once a day.

Other information

store between 20 to 25 C (66 to 77 F)

Inactive ingredients

carbomer, cetyl alcohol, dimethicone, glycerin, glycol stearate, methylparaben, propylene glycol, propylparaben, squalane, triethanolamine, water.

Package Label

Enter section text here